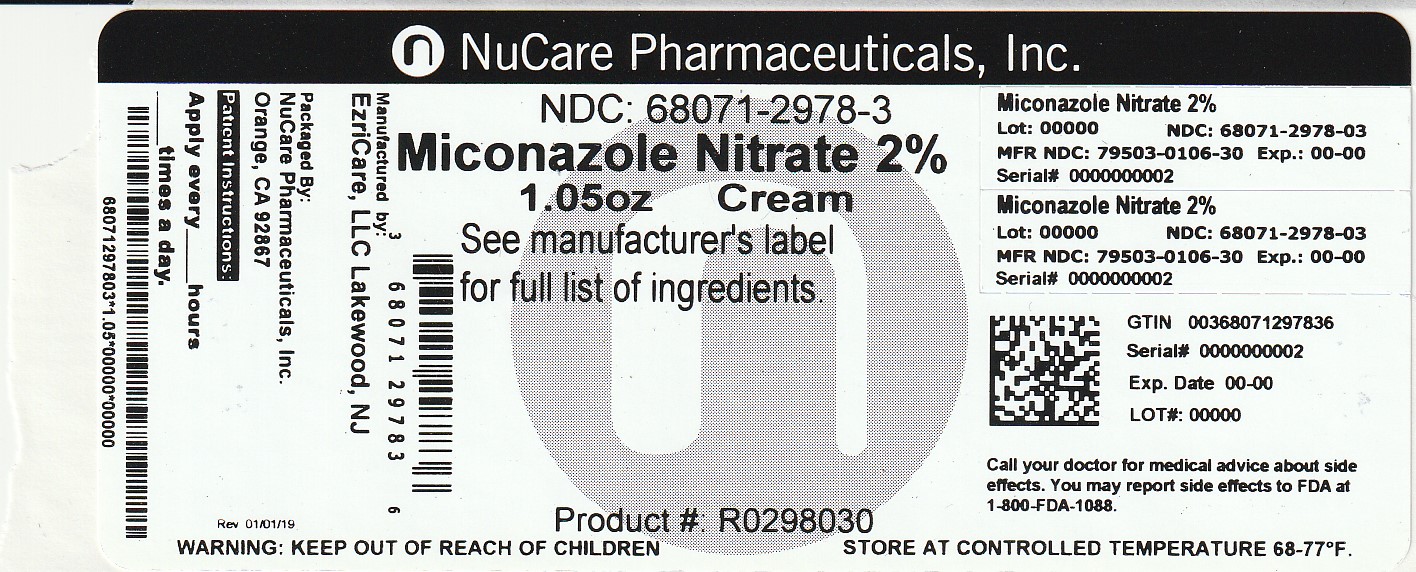 DRUG LABEL: Miconazole Nitrate Cream 2%
NDC: 68071-2978 | Form: CREAM
Manufacturer: NuCare Pharmaceuticals,Inc.
Category: otc | Type: HUMAN OTC DRUG LABEL
Date: 20230417

ACTIVE INGREDIENTS: MICONAZOLE NITRATE 20 mg/1 g
INACTIVE INGREDIENTS: CETOSTEARYL ALCOHOL; CHLOROCRESOL; EDETATE DISODIUM; LIGHT MINERAL OIL; POLYOXYL 20 CETOSTEARYL ETHER; PROPYLENE GLYCOL; WATER; SODIUM PHOSPHATE, DIBASIC, DIHYDRATE; SODIUM PHOSPHATE, MONOBASIC, DIHYDRATE; WHITE PETROLATUM

EZRI CARETM Miconazole Nitrate Cream USP 2%

Active ingredient

Miconazole Nitrate 2%

Purpose

Antifungal

Uses

• For the treatment of most athlete’s foot (tinea pedis), jock itch (tinea cruris), ringworm (tinea corporis)
• Relieves itching, scaling, burning, discomfort and chafing associated with jock itch or itching, burning feet

Warnings

For external use only

Do not use • on children under 2 years of age unless directed by a doctor • for diaper rash

When using this product • avoid contact with the eyes

Stop use and ask a doctor if • irritation occurs • there is no improvement within 2 weeks when used for the treatment of jock itch • there is no improvement within 4 weeks when used for athlete’s foot or ringworm

Keep out of reach of children. If swallowed, get medical help or contact a Poison Control Center right away.

Directions

• Clean the affected area and dry thoroughly. Apply a thin layer of cream over affected area twice daily (morning and night) or as directed by a doctor • Supervise children in the use of this product • For athlete’s foot: Pay special attention to spaces between the toes; wear well-fitting, ventilated shoes, and change shoes and socks at least once daily • For athlete’s foot and ringworm, use daily for 4 weeks • For jock itch, use daily for 2 weeks • If condition persists longer, consult a doctor. • This product is not effective on the scalp or nails

Other information

• Do not use if seal on the tube is damaged or is not visible. To open, unscrew cap, pull tab to remove foil seal • Store at room temperature • See crimp of tube or carton for Lot Number and Expiry Date

Inactive Ingredients

Cetostearyl Alcohol, Chlorocresol, Edetate Disodium, Light Mineral Oil, Macrogol Cetostearyl Ether, Propylene Glycol, Purified Water, Sodium Phosphate Dibasic Dihydrate, Sodium Phosphate Monobasic Dihydrate, White Petrolatum

Questions or comments?

718-502-6610 between 9 am to 4 pm EST, Monday-Friday.

Cures Most Athlete's Foot

Compared to the active ingredient in Micatin®*

Relieves Itching and Burning Sensation Relieves from Cracking and scaling. Grease less and non-staining

*This product is not affiliated with, manufactured by, or produced by the makers or owners of Micatin®

Distributed by:

EzriCare, LLC

Lakewood, NJ

www.EzriCare.com

Made in India